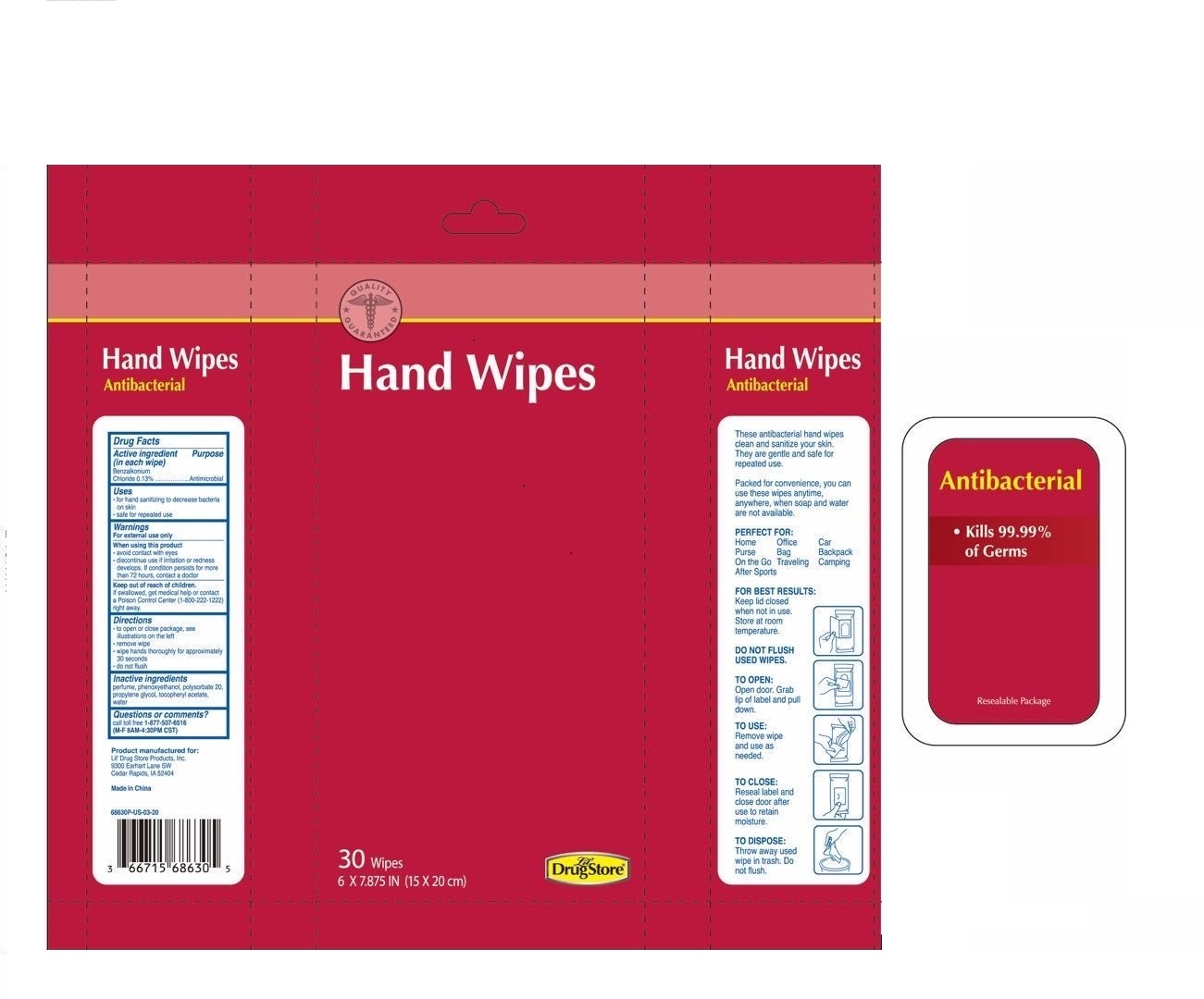 DRUG LABEL: Antibacterial Wipes
NDC: 71927-010 | Form: SWAB
Manufacturer: Orazen Inc
Category: otc | Type: HUMAN OTC DRUG LABEL
Date: 20200518

ACTIVE INGREDIENTS: BENZALKONIUM CHLORIDE 0.13 mg/1 mL
INACTIVE INGREDIENTS: WATER; PROPYLENE GLYCOL; PHENOXYETHANOL; POLYSORBATE 20; .ALPHA.-TOCOPHEROL ACETATE, D-

Drug Facts

Active Ingredient(s)

Benzalkonium Chloride 0.13 % v/v. Purpose: Antiseptic

Purpose

Antibacterial, Wipe

Use

Decrease bacteria on skin. For use when soap and water are not available.

Warnings

For external use only. Flammable. Keep away from heat or flame

Do not use

- in children less than 2 months of age
- on open skin wounds

When using this product keep out of eyes, ears, and mouth. In case of contact with eyes, rinse eyes thoroughly with water.
Stop use and ask a doctor if irritation or rash occurs. These may be signs of a serious condition.
Keep out of reach of children. If swallowed, get medical help or contact a Poison Control Center right away.

Stop use and ask a doctor if irritation or rash occurs. These may be signs of a serious condition.

Keep out of reach of children. If swallowed, get medical help or contact a Poison Control Center right away.

Directions

- Apply to hands
- allow skin to dry without wiping
- Supervise children under 6 years of age when using this product to avoid swallowing.

Other information

- Store between 15-30C (59-86F)
- Avoid freezing and excessive heat above 40C (104F)

Inactive ingredients

Water, Propylene Glycol, Phenoxyethanol, Polysorbate 20, Tocopheryl Acetate, Fragrance

Package Label - Principal Display Panel

30ct NDC: 69821-001-25